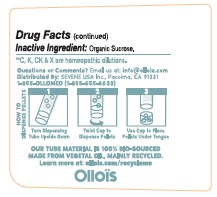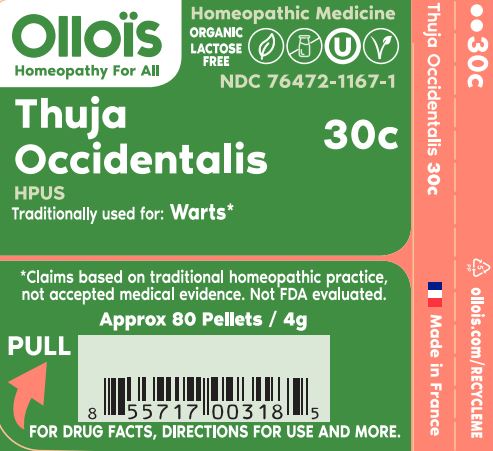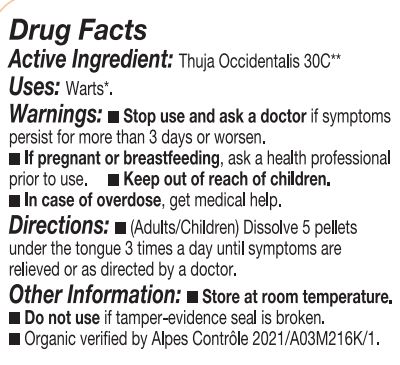 DRUG LABEL: Thuja Occidentalis
NDC: 76472-1167 | Form: PELLET
Manufacturer: SEVENE USA
Category: homeopathic | Type: HUMAN OTC DRUG LABEL
Date: 20240130

ACTIVE INGREDIENTS: THUJA OCCIDENTALIS LEAFY TWIG 30 [hp_C]/1 1
INACTIVE INGREDIENTS: SUCROSE

Sevene USA (as PLD) - Thuja Occidentalis 30c (76472-1167)

ACTIVE INGREDIENT:

HOMEOPATHIC DILUTION OF HPUS THUJA OCCIDENTALIS 30C.

TRADITIONALLY USE FOR:

Warts*

DIRECTIONS:

(adults/children) Dissolve 5 pellets under the tongue 3 times a day until symptoms are relieved or as directed by a physician.

Keep out of reach of children.

PREGNANCY OR BREAST FEEDING

If pregnant or breast-feeding, ask a health professional before use.

WARNINGS:

Stop use and ask a physician if symptoms persist for more than 3 days or worsen.

OTHER INFORMATION:

Store at room temperature.

USE:

Condition listed above or as directed by a physician.

DO NOT USE IF PELLET DISPENSER SEAL IS BROKEN.

INACTIVE INGREDIENT:

Sucrose.

QUESTIONS?

INFO@OLLOIS.COM * WWW.OLLOIS.COM * MADE IN FRANCE. NOT REVIEWED BY THE FDA AND NOT GUARANTEED TO BE EFFECTIVE. THIS HOMEOPATHIS DILUTION MAY NOT BE SUSEPTIBLE TO SCIENTIFIC MEASUREMENT.

USE:

Condition listed above or as directed by a physician.